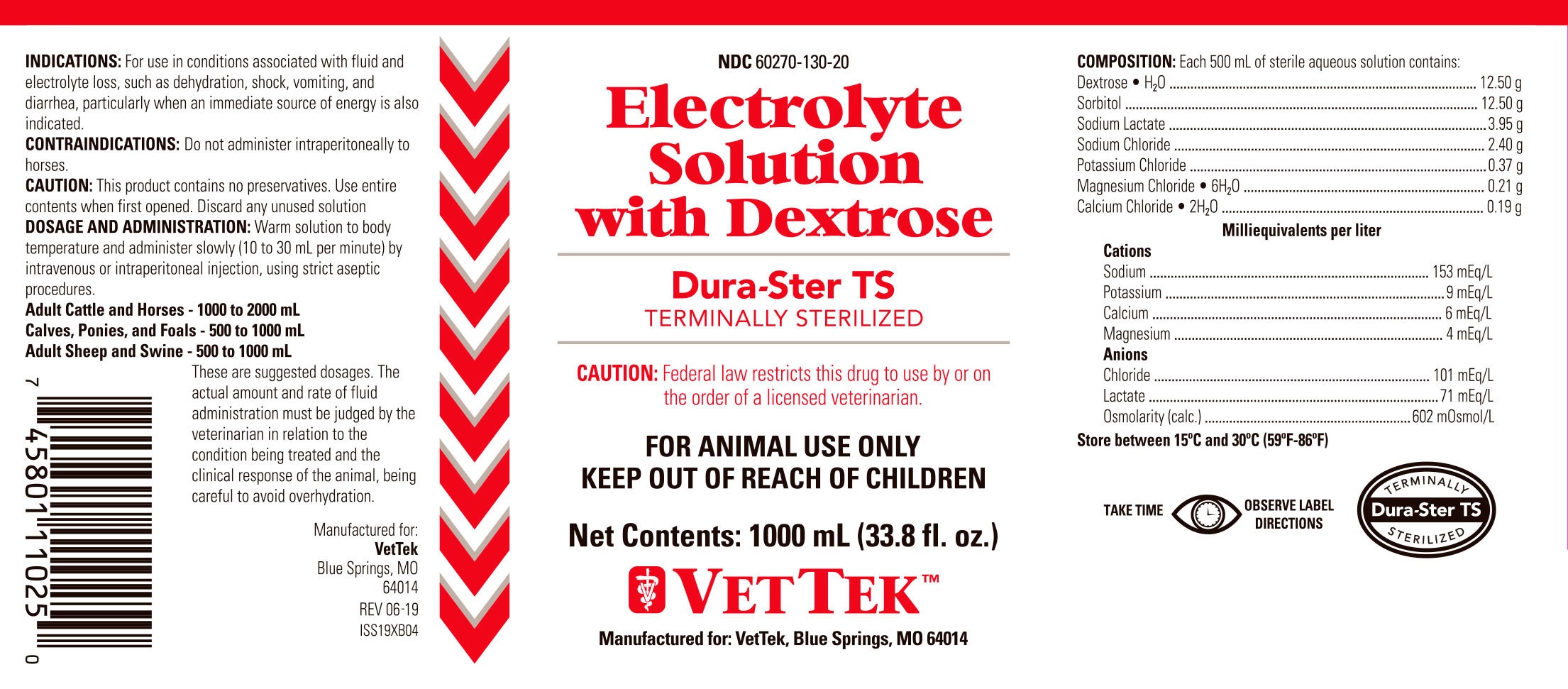 DRUG LABEL: Dura-Ster TS
NDC: 60270-130 | Form: INJECTION, SOLUTION
Manufacturer: VetTek
Category: animal | Type: PRESCRIPTION ANIMAL DRUG LABEL
Date: 20191219

ACTIVE INGREDIENTS: Dextrose Monohydrate 12.50 g/1000 mL; Sorbitol 12.50 g/1000 mL; Sodium Lactate 3.95 g/1000 mL; Sodium Chloride 2.40 g/1000 mL; Potassium Chloride 0.37 g/1000 mL; Magnesium Chloride 0.21 g/1000 mL; Calcium Chloride 0.19 g/1000 mL

ELECTROLYTE SOLUTION WITH DEXTROSE

COMPOSITION

Each 500 mL of sterile aqueous solution contains:

Dextrose.H2O 12.50g

Sorbitol 12.50g

Sodium Lactate 3.95g

Sodium Chloride 2.40g

Potassium Chloride 0.37g

Magnesium Chloride.6H2O 0.21g

Calcium Chloride.2H2O 0.19g

Milliequivalents per liter

Cations

Sodium 153mEq/L

Potassium 9mEq/L

Calcium 6mEq/L

Magnesium 4mEq/L

Anions

Chloride 101 mEq/L

Lactate 71 mEq/L

Osmolarity (calc.) 602 mOsmol/L

INDICATIONS

For use in conditions associated with fluid and electrolyte loss such as dehydration, shock, vomitting, and diarrhea, particularly when an immediate source of energy is also indicated.

CONTRAINDICATIONS

Do not administer intraperitoneally to horses

DOSAGE AND ADMINISTRATION

Warm solution to body temperature and administer slowly (10 to 30 mL per minute) by intravenous or intraperitoneal injections, using strict aseptic procedures.

Adult Cattles and Horses - 1000 to 2000 mL

Calves, Ponies, and Foals - 500 to 1000 mL

Adult, Sheep and Swine - 500 to 1000 mL

These are suggested dosages. The actual amount and rate of fluid administration must be judged by the veterinarian in relation to the condition being treated and the clinical response of the animal, being careful to avoid overhydration

VETERINARY INDICATIONS

FOR ANIMAL USE ONLY

KEEP OUT OF REACH OF CHILDREN

CAUTION:

Federal law restricts this drug to use by or on the order of a licensed veterinarian

STORAGE AND HANDLING

Store between 15oC and 30oC (59oF - 86oF)

SAFE HANDLING WARNING

TAKE TIME OBSERVE LABEL DIRECTIONS

Manufactured for:

VetTex

Blue Springs, MO

64014

REV 6-19

ISS19XB04

Principal Display Panel

NDC 60270-130-20

Electrolyte Solution With Dextrose

Durs-Ster TS

TERMINALLY STERILIZED